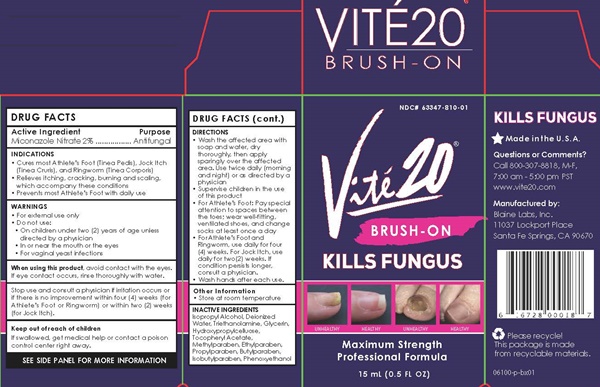 DRUG LABEL: Vite20
NDC: 63347-810 | Form: LIQUID
Manufacturer: Blaine Labs Inc.
Category: otc | Type: HUMAN OTC DRUG LABEL
Date: 20241224

ACTIVE INGREDIENTS: MICONAZOLE NITRATE 0.30 mg/15 mL
INACTIVE INGREDIENTS: ISOPROPYL ALCOHOL; WATER; TROLAMINE; GLYCERIN; HYDROXYPROPYL CELLULOSE, UNSPECIFIED; .ALPHA.-TOCOPHEROL ACETATE; METHYLPARABEN; ETHYLPARABEN; PROPYLPARABEN; BUTYLPARABEN; ISOBUTYLPARABEN; PHENOXYETHANOL

Vite20 - 810

DRUG FACTS Active Ingredient

Miconazole Nitrate 2%

Purpose

Antifungal

Keep out of reach of children. If swallowed, get medical help or contact a poison control center right away.

INDICATIONS

- Cures most Athlete's Foot (Tinea Pedis), Jock Itch (Tinea Cruris), and Ringworm (Tinea Corporis)
- Relieves Itching, cracking, burning and scaling. which accompany these conditions
- Prevents most Athlete's Foot with daily use

WARNINGS

- For external use only
- Do not use :
- On children under two (2) years of age unless directed by a physician
- In or near the mouth or the eyes
- For vaginal yeast infections

When using this product

avoid contact with the eyes. If contact occurs, rinse thoroughly with water.

Stop use and consult a physician

if irritation occurs or if there is no improvement within four (4) weeks (for Athlete's Foot or Ringworm) or within two (2) weeks (for Jock Itch)

DIRECTIONS

- Was the affected area with soap and water, dry thorougly, then apply sparingly over the affected area. Use twice daily (morning and night) or as directed by a physician
- Supervise children in the use of this product
- For Athlete's Foot and Ringworm, use daily for four (4) weeks. For Jock Itch, use daily for two (2) weeks. If condition persists longer, consult a physician
- Wash hands after each use.

Other Information

- Store at room temperature

INACTIVE INGREDIENTS

Isopropyl Alcohol, Deionized Water, Triethanokamine, Glycerin, Hydroxypropylcelluose, Tocopheryl Acetate, Methylparaben, Ethylparaben, Propylparaben, Butylparaben, Isobutylparaben, Phenoxyethanol

Vite20 product label

VITÉ 20

BRUSH - ON

NDC# 63347-810-01

Vité20®

BRUSH-ON

KILLS FUNGUS

Maxium Strength

Professional Formula

15 mL (0.5 FL OZ)

SEE SIDE PANEL FOR MORE INFORMATION

KILLS FUNGUS

*Made in the U.S.A.

Questions or Comments?

Call 800-307-8818 M-F

7:00 am - 5:00 pm PST

www.vite20.com

Manufactured by:

Blaine Labs, Inc.

11037 Lockport Place

Santa Fe Springs, CA 90670

Please recycle!

This package is made from recyclable materials

06100-p-bx01

res